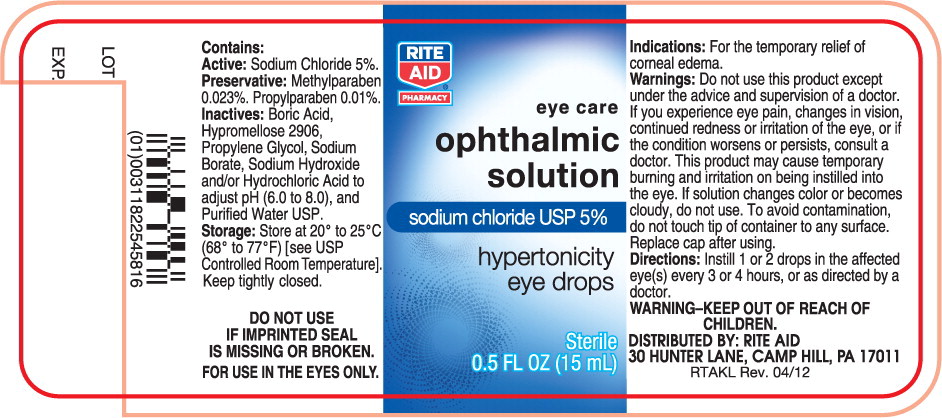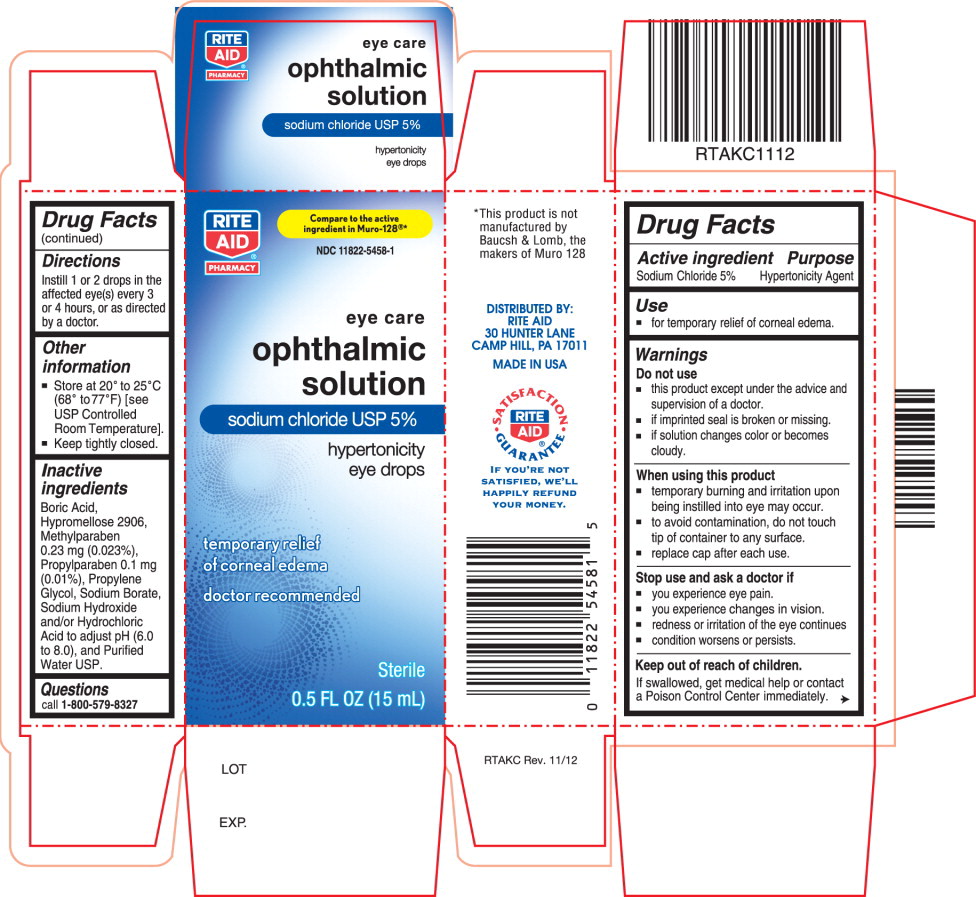 DRUG LABEL: Sodium Chloride
NDC: 11822-5458 | Form: SOLUTION/ DROPS
Manufacturer: Rite Aid Corporation
Category: otc | Type: HUMAN OTC DRUG LABEL
Date: 20220127

ACTIVE INGREDIENTS: Sodium Chloride 50 mg/1 mL
INACTIVE INGREDIENTS: Boric Acid; Hypromelloses; Propylene Glycol; Sodium Borate; Sodium Hydroxide; Hydrochloric Acid; Water; Methylparaben; Propylparaben

Drug Facts

Active ingredient

Sodium Chloride 5%

Purpose

Hypertonicity Agent

Use

- for temporary relief of corneal edema.

Warnings

Do not use

- this product except under the advice and supervision of a doctor.
- if imprinted seal is broken or missing.
- if solution changes color or becomes cloudy.

When using this product

- temporary burning and irritation upon being instilled into eye may occur.
- to avoid contamination, do not touch tip of container to any surface.
- replace cap after each use.

Stop use and ask a doctor if

- you experience eye pain.
- you experience changes in vision.
- redness or irritation of the eye continues
- condition worsens or persists.

Keep out of reach of children.

If swallowed, get medical help or contact a Poison Control Center immediately.

Directions

Instill 1 or 2 drops in the affected eye(s) every 3 or 4 hours, or as directed by a doctor.

Other information

- Store at 20° to 25°C (68° to77°F) [see USP Controlled Room Temperature].
- Keep tightly closed.

Inactive ingredients

Boric Acid, Hypromellose 2906, Methylparaben 0.23 mg (0.023%), Propylparaben 0.1 mg (0.01%), Propylene Glycol, Sodium Borate, Sodium Hydroxide and/or Hydrochloric Acid to adjust pH (6.0 to 8.0), and Purified Water USP.

Questions

call 1-800-579-8327

Principal Display Panel Text for Container Label:

RITE
AID®
PHARMACY

eye care
ophthalmic
solution
sodium chloride USP 5%
hypertonicity
eye drops
Sterile
0.5 FL OZ (15 mL)

Principal Display Panel Text for Carton Label:

RITE Compare to the active
AID® ingredient in Muro-128®*
PHARMACY NDC 11822-5458-1
eye care
ophthalmic
solution
sodium chloride USP 5%
hypertonicity
eye drops
temporary relief
of corneal edema
doctor recommended
Sterile
0.5 FL OZ (15 mL)